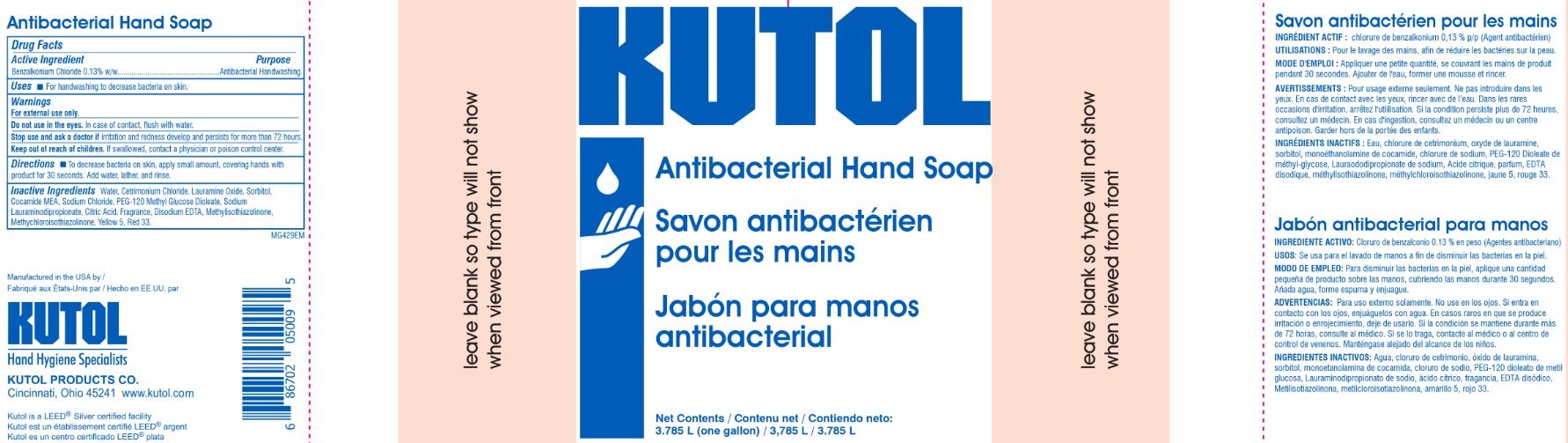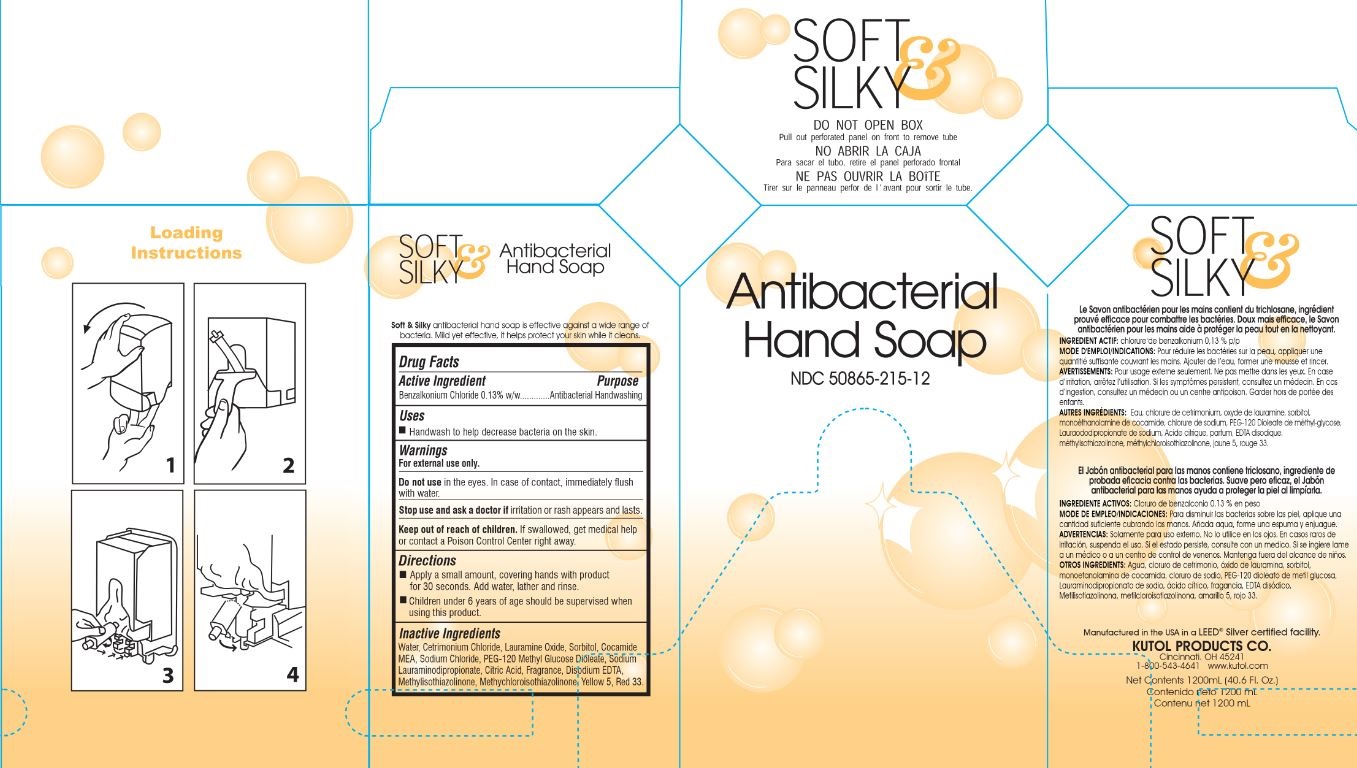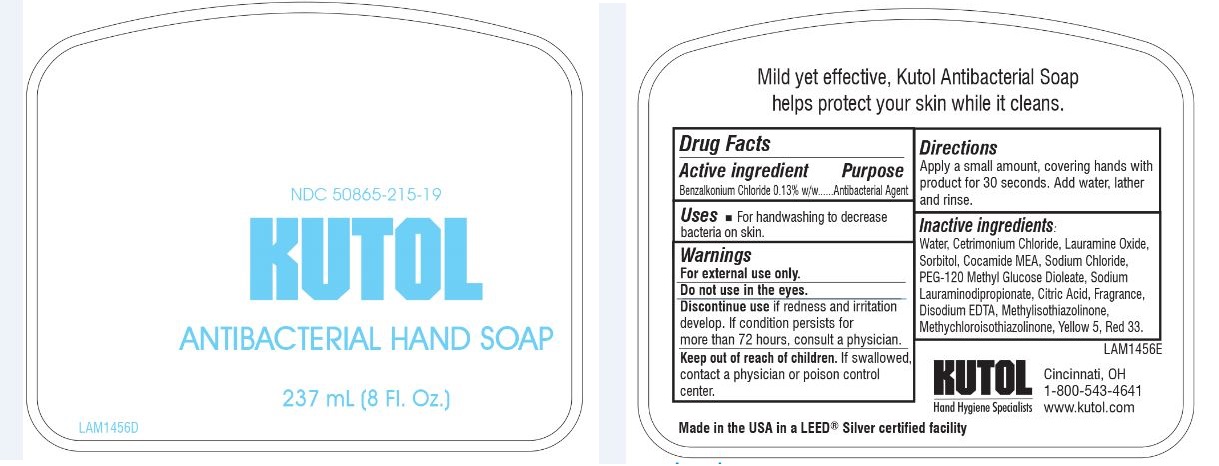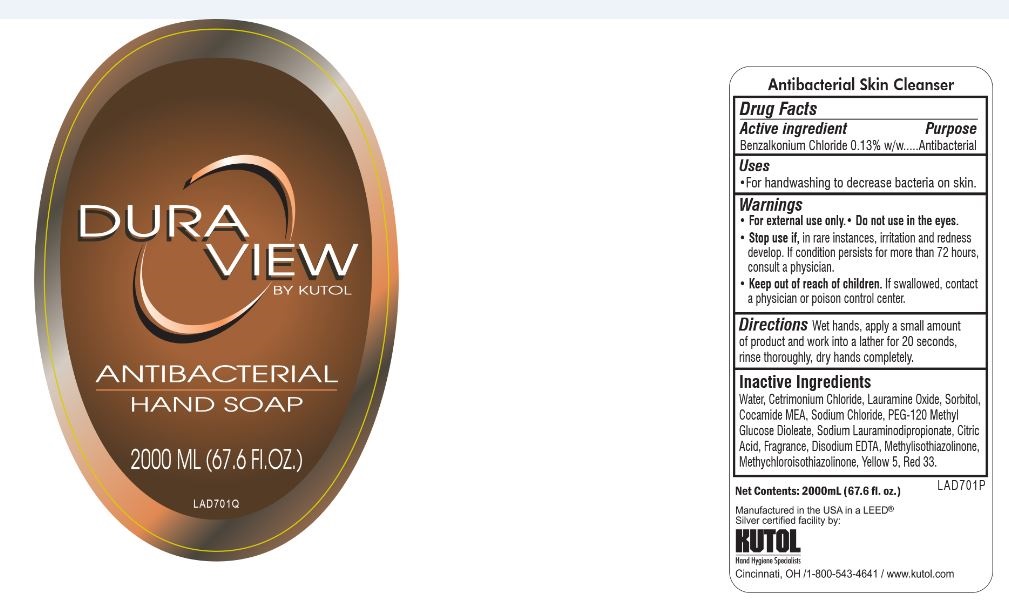 DRUG LABEL: Antibacterial Hand Cleanser
NDC: 50865-215 | Form: SOAP
Manufacturer: Kutol Products Company
Category: otc | Type: HUMAN OTC DRUG LABEL
Date: 20230828

ACTIVE INGREDIENTS: BENZALKONIUM CHLORIDE 0.013 mg/1 mL
INACTIVE INGREDIENTS: WATER; SODIUM CHLORIDE; CETRIMONIUM CHLORIDE; LAURAMINE OXIDE; SORBITOL; COCO MONOETHANOLAMIDE; SODIUM LAURIMINODIPROPIONATE; D&C RED NO. 33; FD&C YELLOW NO. 5; PEG-120 METHYL GLUCOSE DIOLEATE; METHYLISOTHIAZOLINONE; METHYLCHLOROISOTHIAZOLINONE; EDETATE DISODIUM ANHYDROUS; CITRIC ACID MONOHYDRATE

Kutol F215F

Active Ingredient

Benzalkonium Chloride 0.13% w/w

Purpose

Antibacterial Handwashing

Keep out of reach of children. If swallowed, get medical help or contact a poison control center right away.

INDICATIONS AND USAGE

Uses Handwash to decrease bacteria on the skin.

Directions

- Apply a small amount, covering hands with product for 30 seconds. Add water, lather and rinse.
- Children under 6 years of age should be supervised when using this product.

Warnings

For external use only.

Do not usein the eyes. In case of contact, immediately flush with water.

Stop use and ask a doctor if redness and irritation appears and lasts.

Inactive Ingredients

water, cetrimonium chloride, lauramine oxide, sorbitol, cocamide MEA, sodium chloride, PEG-120 methyl glucose dioleate, sodium lauraminodipropionate, citric acid, fragrance, disodium EDTA, methyisothiazolinone, methylchloroisothiazolinone, yellow 5, red 33